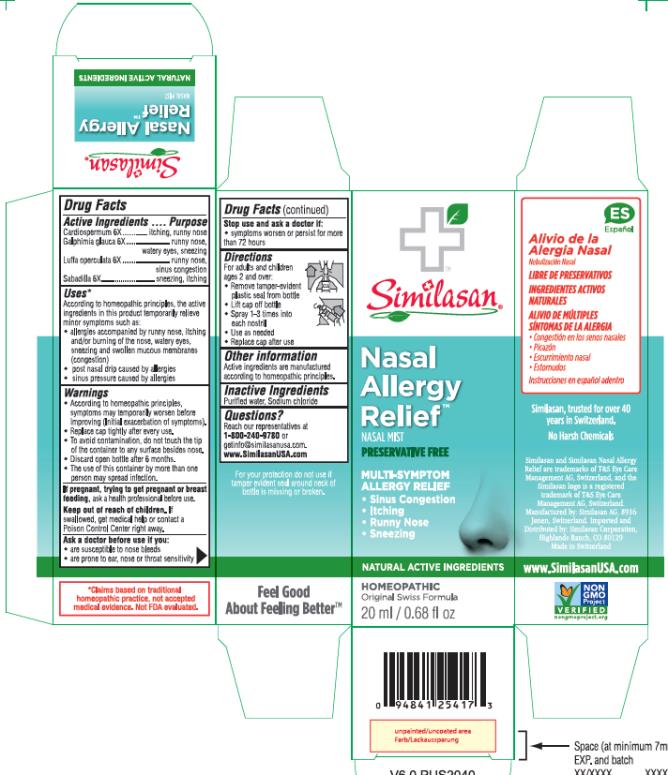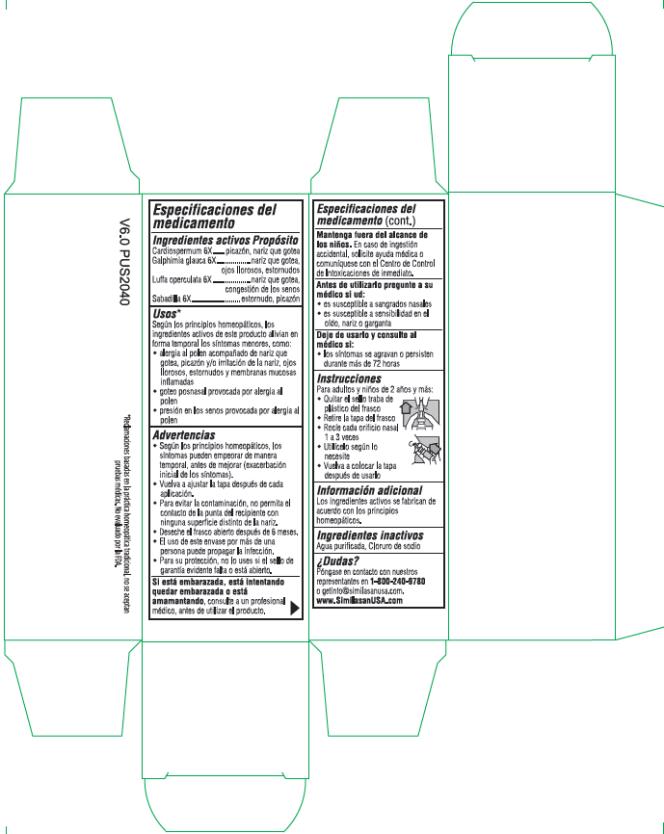 DRUG LABEL: Nasal Allergy Relief
NDC: 53799-241 | Form: SPRAY
Manufacturer: Similasan AG
Category: homeopathic | Type: HUMAN OTC DRUG LABEL
Date: 20211101

ACTIVE INGREDIENTS: CARDIOSPERMUM HALICACABUM FLOWERING TOP 6 [hp_X]/20 mL; GALPHIMIA GLAUCA FLOWERING TOP 6 [hp_X]/20 mL; LUFFA OPERCULATA FRUIT 6 [hp_X]/20 mL; SCHOENOCAULON OFFICINALE SEED 6 [hp_X]/20 mL
INACTIVE INGREDIENTS: WATER; SODIUM CHLORIDE

Nasal Allergy Relief

Drug Facts

Active ingredients

Cardiospermum 6X

Purpose

itching, runny nose

Active Ingredient

Galphimia glauca 6X

Purpose

runny nose, watery eyes, sneezing

Active Ingredient

Luffa operculata 6X

Purpose

runny nose, sinus congestion

Active Ingredient

Sabadilla 6X

Purpose

sneezing, itching

Uses*:

According to homeopathic principles, the active ingredients in this product temporarily relieve minor symptoms such as:

- allergies accompanied by runny nose, itching and/or burning of the nose, watery eyes, sneezing and swollen mucous membranes (congestion)
- post nasal drip caused by allergies
- sinus pressure caused by allergies

Warnings:

- According to homeopathic principles, symptoms may temporarily worsen before improving (Initial exacerbation of symptoms).
- Replace cap tightly after every use.
- To avoid contamination, do not touch the tip of the container to any surface besides nose.
- Discard open bottle after 6 months.
- The use of this container by more than one person may spread infection.

If pregnant, trying to get pregnant or breast feeding,

ask a health professional before use.

Keep out of reach of children.

If swallowed, get medical help or contact a Poison Control Center right away.

Ask a doctor before use if you:

- are susceptible to nose bleeds
- are prone to ear, nose or throat sensitivity

Stop use and ask a doctor if:

- symptoms worsen or persist for more than 72 hours

Directions

For adults and children ages 2 and over:

- Remove tamper-evident plastic seal from bottle
- Lift cap off bottle
- Spray 1-3 times into each nostril
- Use as needed
- Replace cap after use

Other information:

Active ingredients are manufactured according to homeopathic principles.

Inactive Ingredients:

Purified water, Sodium chloride

Questions?

Reach our representatives at 1-800-240-9780 or getinfo@similasanusa.com.
www.SimilasanUSA.com

PRINCIPAL DISPLAY PANEL

Similisan
Nasal Allergy Relief
NASAL MIST
PRESERVATIVE FREE
20 ml / 0.68 fl oz